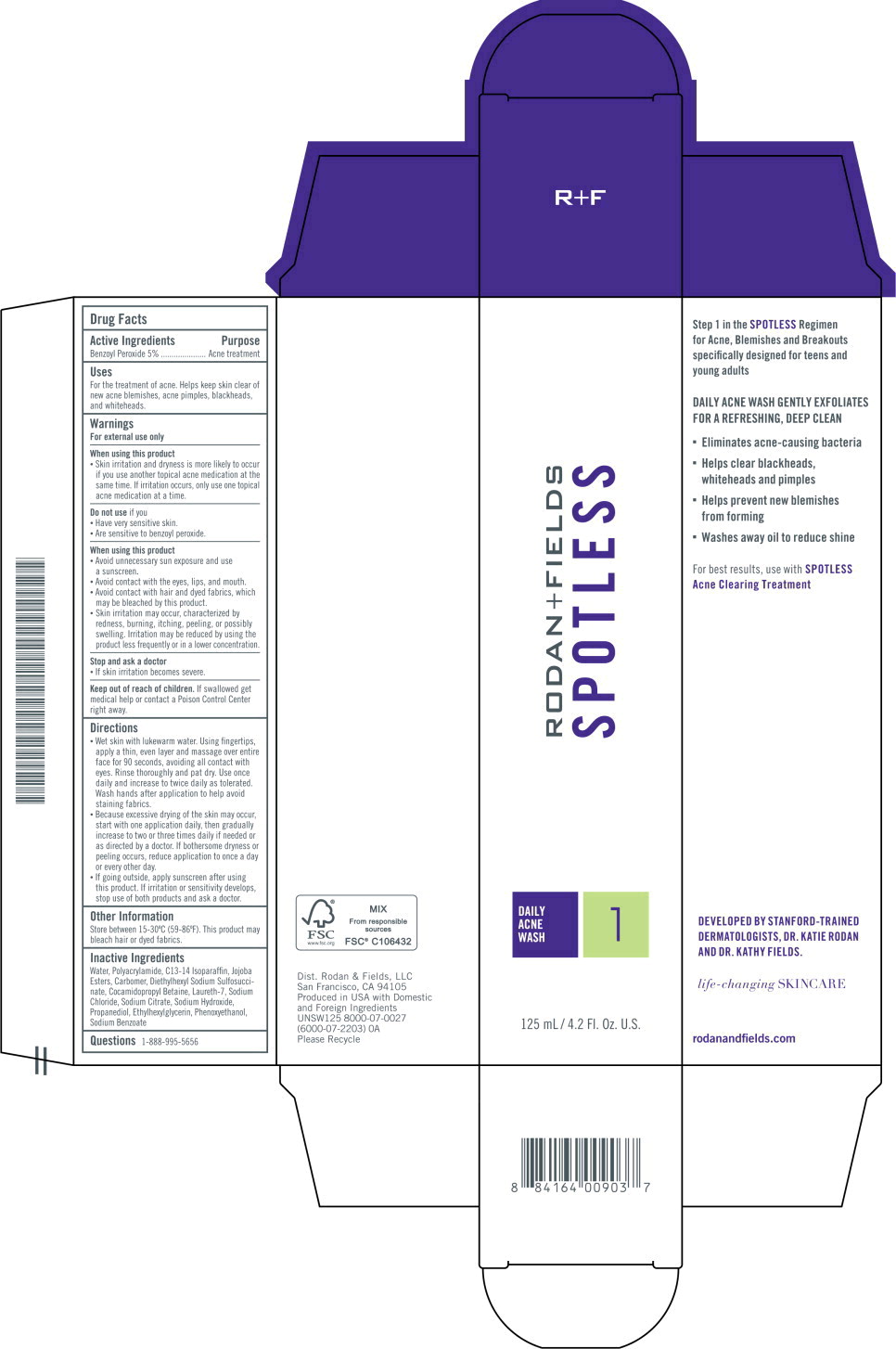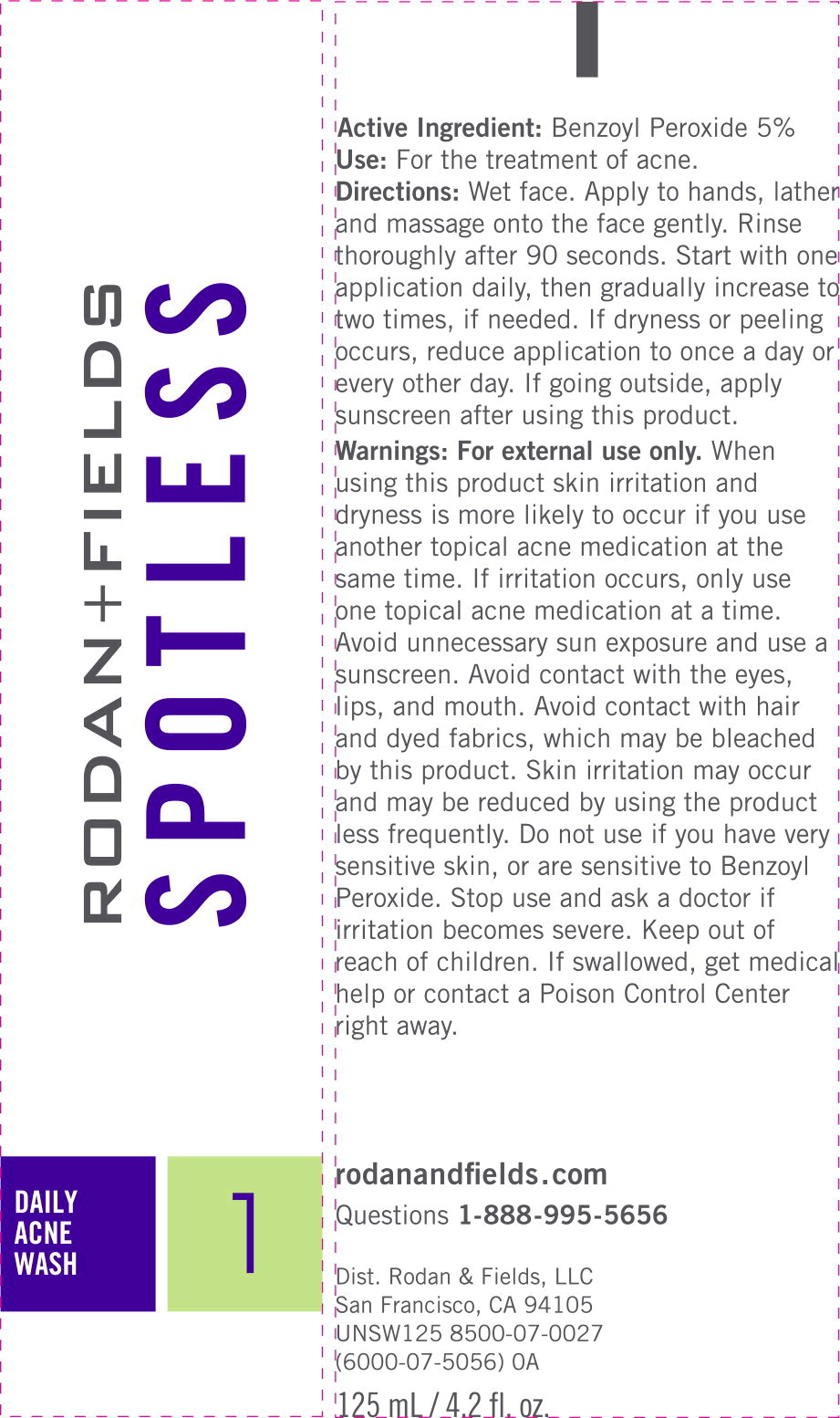 DRUG LABEL: SPOTLESS Daily Acne Wash
NDC: 14222-1610 | Form: CREAM
Manufacturer: Rodan & Fields
Category: otc | Type: HUMAN OTC DRUG LABEL
Date: 20260204

ACTIVE INGREDIENTS: BENZOYL PEROXIDE 0.05 g/1 mL
INACTIVE INGREDIENTS: WATER; POLYACRYLAMIDE (10000 MW); C13-14 ISOPARAFFIN; CARBOXYPOLYMETHYLENE; COCAMIDOPROPYL BETAINE; DOCUSATE SODIUM; ETHYLHEXYLGLYCERIN; HYDROGENATED JOJOBA OIL, RANDOMIZED; LAURETH-7; PHENOXYETHANOL; PROPANEDIOL; SODIUM BENZOATE; SODIUM CHLORIDE; SODIUM CITRATE, UNSPECIFIED FORM; SODIUM HYDROXIDE

Drug Facts

Active ingredient

Benzoyl peroxide 5%

Purpose

Acne treatment

Uses

- for the treatment of acne
- helps keep skin clear of new acne blemishes, acne pimples, blackheads and whiteheads

Warnings

For external use only

Do not use if you

- have very sensitive skin
- are sensitive to benzoyl peroxide

When using this product

- skin irritation may occur, characterized by redness, burning, itching, peeling or possibly swelling. Irritation may be reduced by using the product less frequently or in a lower concentration.
- skin irritation and dryness is more likely to occur if you use another topical acne medication at the same time. If irritation occurs, only use one topical acne medication at a time.
- avoid unnecessary sun exposure and use a sunscreen
- avoid contact with the eyes, lips and mouth
- avoid contact with hair and dyed fabrics, which may be bleached by this product

Stop use and ask a doctor if

- irritation becomes severe

Keep out of reach of children. If swallowed, get medical help or contact a Poison Control Center right away.

Directions

- wet skin with lukewarm water
- using fingertips, apply a thin, even layer and massage over entire face for 90 seconds, avoiding all contact with eyes
- rinse thoroughly and pat dry
- use once daily and increase to twice daily as tolerated
- wash hands after application to help avoid staining fabrics
- because excessive drying of the skin may occur, start with one application daily, then gradually increase to two or three times daily if needed or as directed by a doctor
- if bothersome dryness or peeling occurs, reduce application to once a day or every other day
- if going outside, apply sunscreen after using this product. If irritation or sensitivity develops, stop use of both products and ask a doctor.

Other information

store between 15-30°C (59-86°F)

Inactive ingredients

water, polyacrylamide, C13-14 isoalkane, jojoba esters, carbomer, diethylhexyl sodium sulfosuccinate, cocamidopropyl betaine, laureth-7, sodium chloride, sodium citrate, sodium hydroxide, propanediol, ethylhexylglycerin, phenoxyethanol, sodium benzoate

Questions?

1-888-995-5656

Principal Display Panel - 125 mL Carton Label

RODAN+FIELDS
SPOTLESS

DAILY
ACNE
WASH

1

125 mL/4.2 Fl. Oz. U.S.

Principal Display Panel - 125 mL Tube Label

RODAN+FIELDS
SPOTLESS

DAILY
ACNE
WASH

1